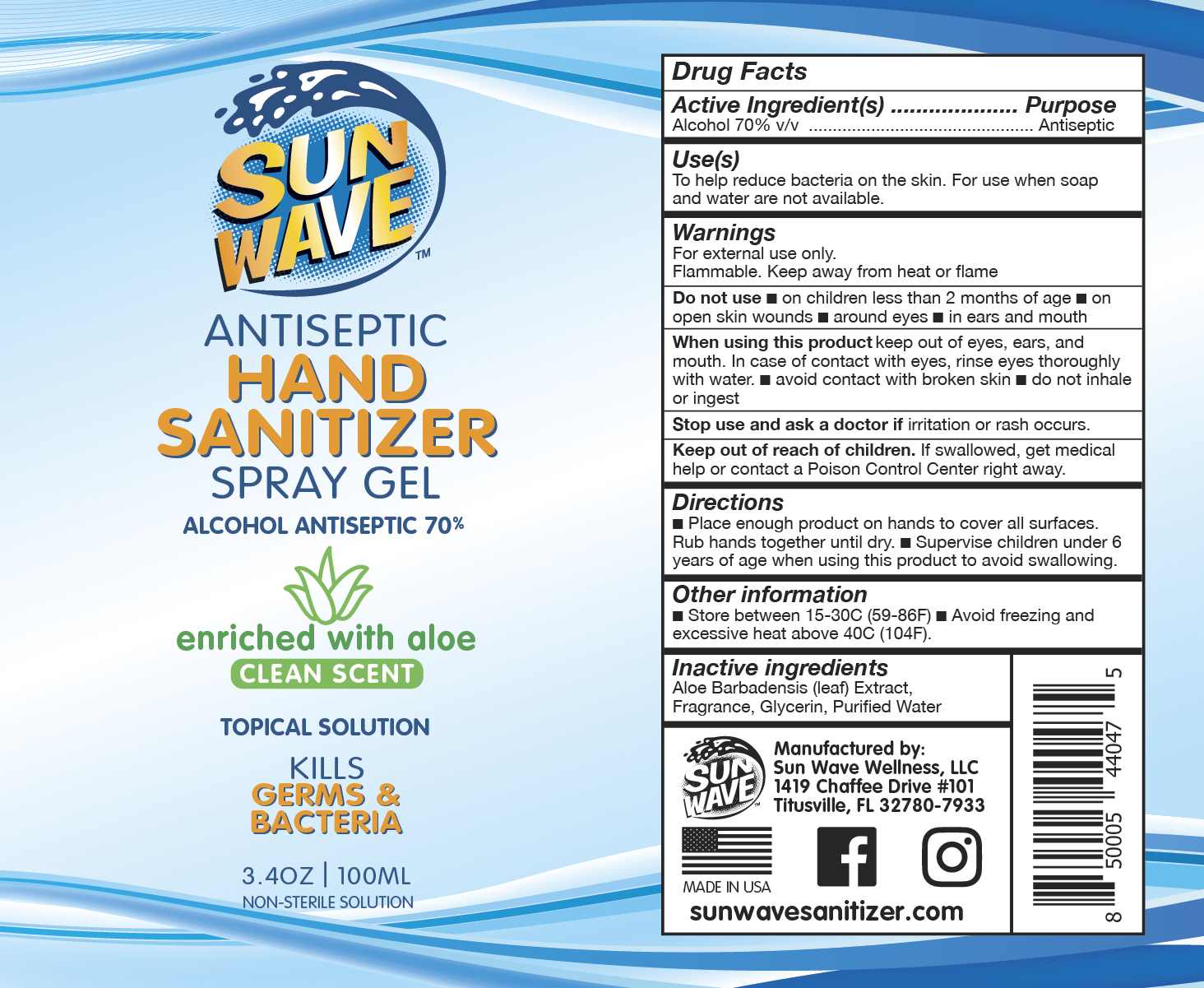 DRUG LABEL: HAND SANITIZER
NDC: 75023-002 | Form: LIQUID
Manufacturer: SUN WAVE WELLNESS, LLC
Category: otc | Type: HUMAN OTC DRUG LABEL
Date: 20200826

ACTIVE INGREDIENTS: ISOPROPYL ALCOHOL 70 mL/100 mL
INACTIVE INGREDIENTS: LIMONENE, (+)- 1 mL/100 mL; WATER 26 mL/100 mL; GLYCERIN 2 mL/100 mL; ALOE VERA LEAF 1 mL/100 mL

VERSION 2: CORRECTION
CORRECTION: (1) LABEL IMAGE CORRECTION
CONSUMER HAND SANITIZER; NON-EMERGENCY; ISOPROPYL ALCHOL (IPA) = DEFERRED GRASE ACTIVE INGREDIENT DETERMINATION EFFECTIVE APRIL 13, 2020; PART333E FOR OTC HAND RUB SANTIZERS (CONSUMER)

Use(s)

To help reduce bacteria on the skin. For use when soap and water are not available.

Active Ingredient

Alcohol 70% v/v

Warnings

For external use only.

Flammable. Keep away from heat or flame.

Do not use

- on children less than 2 months of age
- on open skin wounds
- around eyes
- in ears and mouth

When using this product

keep out of eyes, ears, and mouth.

Incase of contact with eyes, rinse eyes thoroughly with water.

- avoid contact with broken skin
- do not inhale or ingest

Stop use and ask a doctor if

irritation or rash occurs.

Keep out of reach of children.

If swallowed, get medical help or contact a Poison Control Center right away.

Purpose

Antiseptic

Directions

- Place enough product on hands to cover all surfaces. Rub hands together until dry.
- Supervise children under 6 years of age when using this product to avoid swallowing.

Other information

- Store between 15-30C (59-86F)
- Avoid freezing and exessive heat above 40C (104F)

Inactive ingredients

Aloe Barbadenisis (leaf) Extract, Fragrance, Glycerin, Purified Water

Manufactured by:

Sun Wave Wellness, LLC

1419 Chaffee Drive #101

Titusville, FL 32780-7933

sunwavesanitizer.com